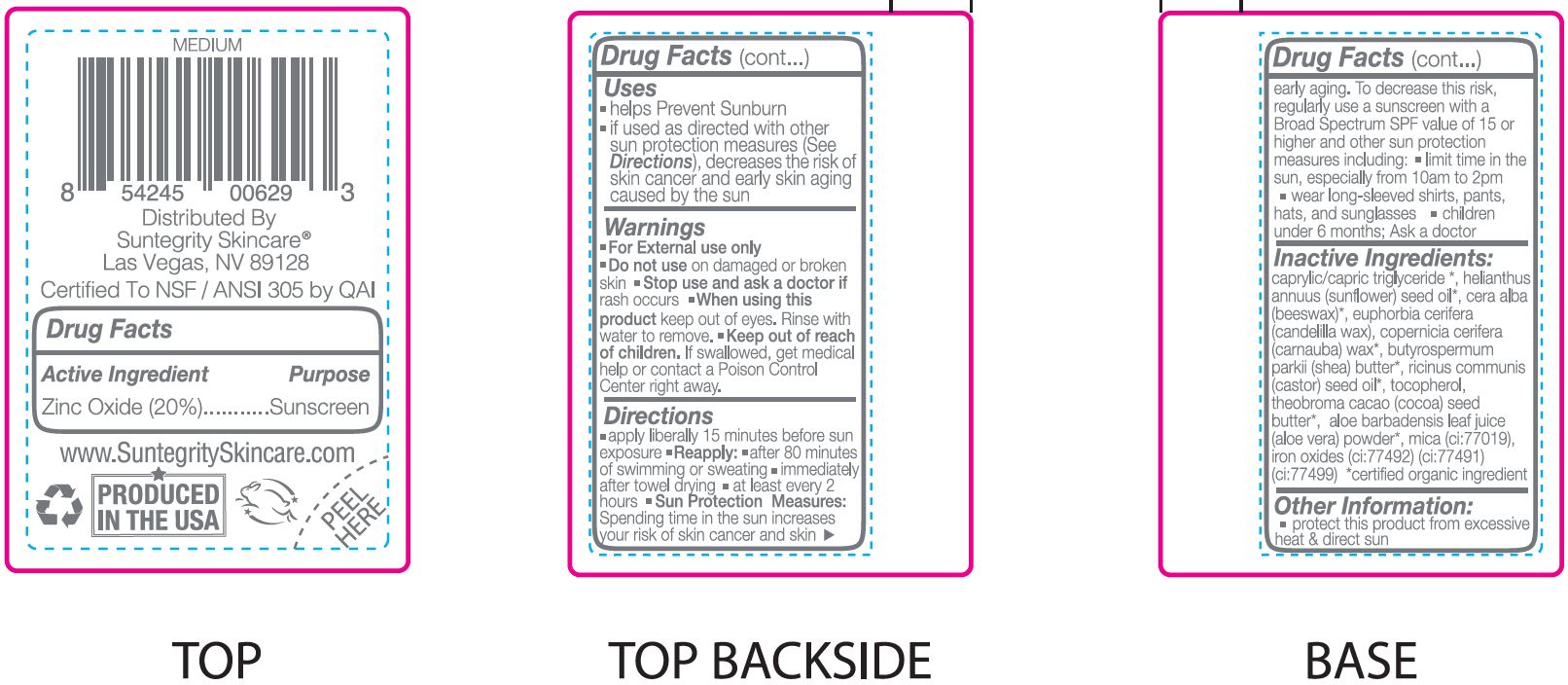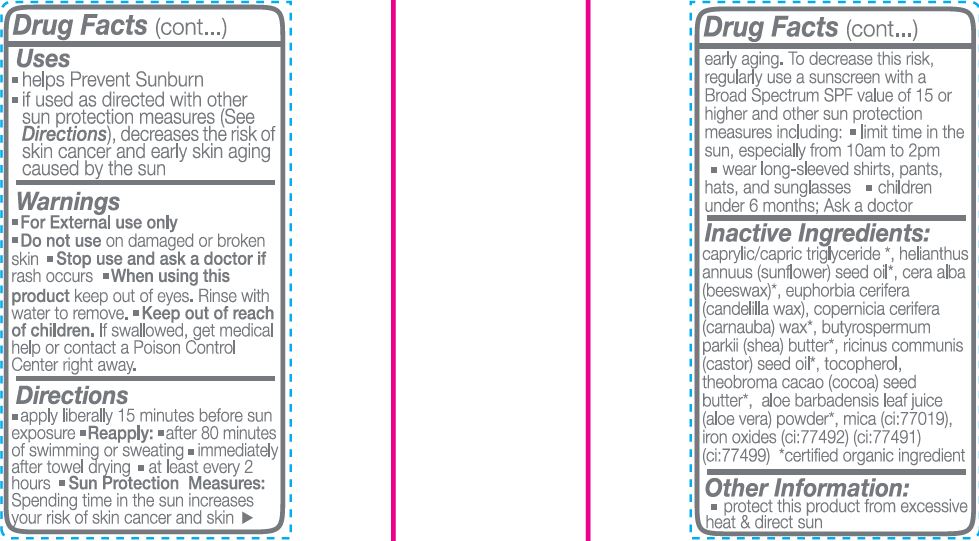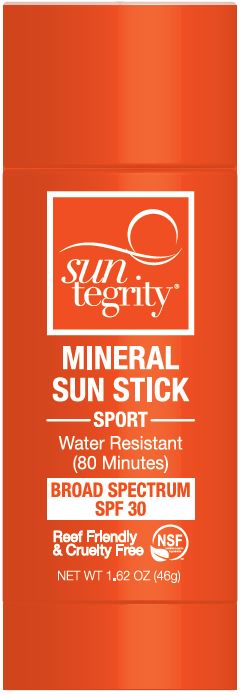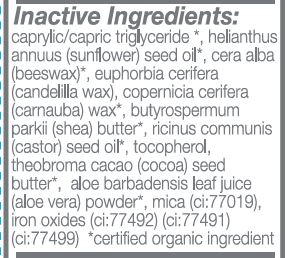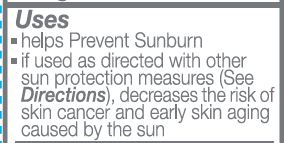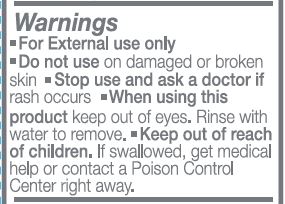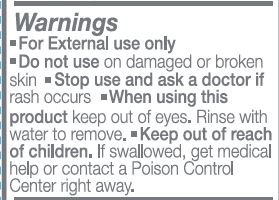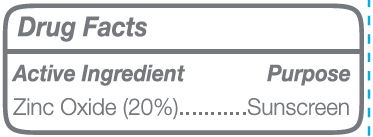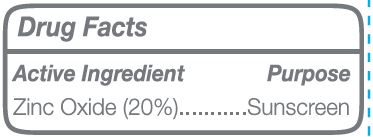 DRUG LABEL: Sunscreen
NDC: 62932-218 | Form: OINTMENT
Manufacturer: Private Label Select Ltd CO
Category: otc | Type: HUMAN OTC DRUG LABEL
Date: 20200715

ACTIVE INGREDIENTS: ZINC OXIDE 20 g/100 g
INACTIVE INGREDIENTS: .BETA.-TOCOPHEROL; CASTOR OIL; FERRIC OXYHYDROXIDE; MEDIUM-CHAIN TRIGLYCERIDES; SUNFLOWER OIL; .ALPHA.-TOCOPHEROL, D-; .GAMMA.-TOCOPHEROL; MICA; CARNAUBA WAX; SHEA BUTTER; ALOE VERA LEAF; .DELTA.-TOCOPHEROL; COCOA BUTTER; WHITE WAX; CANDELILLA WAX; FERROSOFERRIC OXIDE; FERRIC OXIDE RED

Suntegrity, Mineral Sun Stick, SPF 30 - Tinted Medium